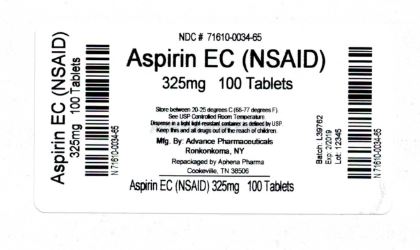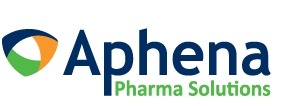 DRUG LABEL: Aspirin
NDC: 71610-034 | Form: TABLET
Manufacturer: Aphena Pharma Solutions - Tennessee, LLC
Category: otc | Type: HUMAN OTC DRUG LABEL
Date: 20180218

ACTIVE INGREDIENTS: ASPIRIN 325 mg/1 1
INACTIVE INGREDIENTS: CROSCARMELLOSE SODIUM; D&C YELLOW NO. 10; FD&C YELLOW NO. 6; METHACRYLIC ACID; POLYETHYLENE GLYCOL 1000; PROPYLENE GLYCOL; POVIDONE; SODIUM LAURYL SULFATE; STARCH, CORN; STEARIC ACID; TALC; TITANIUM DIOXIDE; HYPROMELLOSES

ENTERIC COATED ASPIRIN 325mg

Active Ingredient

(in each tablet)

Aspirin 325 mg (NSAID) *

*nonsteroidal anti-inflammatory drug

Purpose

Pain reliever/ Fever Reducer

Uses

temporarily relieves

- headache
- menstrual pain
- muscle pain
- toothache
- minor pain or arthritis
- pain and fever of colds

Warnings

Reye’s Syndrome: Children and teenagers who have or are recovering from chicken pox or flu-like symptoms should not use this product. When using this product, if changes in behavior with nausea and vomiting occur, consult a doctor because these symptoms could be an early signs of Reye’s syndrome, a rare but serious illness.

Allergy Alert: Aspirin may cause a severe allergic reaction which may include

- hives
- asthma (wheezing)
- shock
- facial swelling
  Stomach Bleeding Warning: This product contains an NSAID, which may cause severe stomach bleeding. The chance is higher if you
- are age 60 or older
- have had stomach ulcers or bleeding problems
- take a blood-thinning (anticoagulant) or steroid drug
- takes other drugs containing prescription or nonprescription NSAIDs (ibuprofen, naproxen, others)
- takes more or for a longer time than directed
- have 3 or more alcoholic drinks every day while using this product.
  Do not use
- if you have ever had an allergic reaction to any other pain reliever / fever reducer
  Ask a doctor before use if
- stomach bleeding warning applies to you
- you have a history of stomach problems, such as heartburn
- you have high blood pressure, heart disease, lever cirrhosis, or kidney disease
- you are taking a diuretic
- you have asthma
  Ask a doctor or pharmacist before use if you are
- taking a prescription drug for diabetes, gout or arthritis
- taking any other drug
- under a doctor’s care for any serious condition
  Stop use and ask a doctor if
- you experiences any of the following signs of stomach bleeding:
- feel faint
- vomit blood
- have bloody or black stools
- have stomach pain that does not get better
- pain gets worse or lasts more than 10 days
- fever gets worse or lasts more than 3 days
- redness or swelling is present in the painful area
- any new symptoms appear
- ringing in the ears or a loss of hearing occurs
  If pregnant or breast-feeding, ask a health professional before use. It is especially important not to use aspirin during the last 3 months of pregnancy unless definitely directed to do so by a doctor because it may cause problems in the unborn child or complications during delivery.

Keep out of reach of children.

In case of overdose, get medical help or contact a Poison Control Center right away.

Directions

DRINK A FULL GLASS OF WATER WITH EACH DOSE

- adults and children 12 years and over : 1-2 tablets every 4 hours while symptoms last, but not more than 12 tablets in 24 hours.
- Children under 12 years: ask a doctor

Other Information

- avoid excessive heat or humidity
- store at 15-30 °C (59-86 °F)

Inactive Ingredients

croscarmellose sodium, D&C Yellow #10 (Al-Lake), FD&C yellow #6 (Al-Lake), HPMC, methacrylic acid copolymer, polyethylene glycol, propylene glycol, PVP, sodium lauryl sulfate, starch, stearic acid, talc, titanium dioxide

Questions or Comments

Call 631-981-4600, 8.30am – 4.30 pm ET Monday-Friday

TAMPER EVIDENT: DO NOT USE IF IMPRINTED SAFETY SEAL UNDER CAP IS BROKEN OR MISSING

Manufactured by: Advance Pharmaceutical, Inc. Holtsville, NY 11742

Repackaging Information

Please reference the How Supplied section listed above for a description of individual tablets. This drug product has been received by Aphena Pharma - TN in a manufacturer or distributor packaged configuration and repackaged in full compliance with all applicable cGMP regulations. The package configurations available from Aphena are listed below:

Count | 325mg
100 | 71610-034-65

Store between 20°-25°C (68°-77°F). See USP Controlled Room Temperature. Dispense in a tight light-resistant container as defined by USP. Keep this and all drugs out of the reach of children.

Repackaged by:
Cookeville, TN 38506
20180218JH

PRINCIPAL DISPLAY PANEL - 325mg

NDC 71610-034 - Aspirin EC (NSAID) 325mg - Rx Only